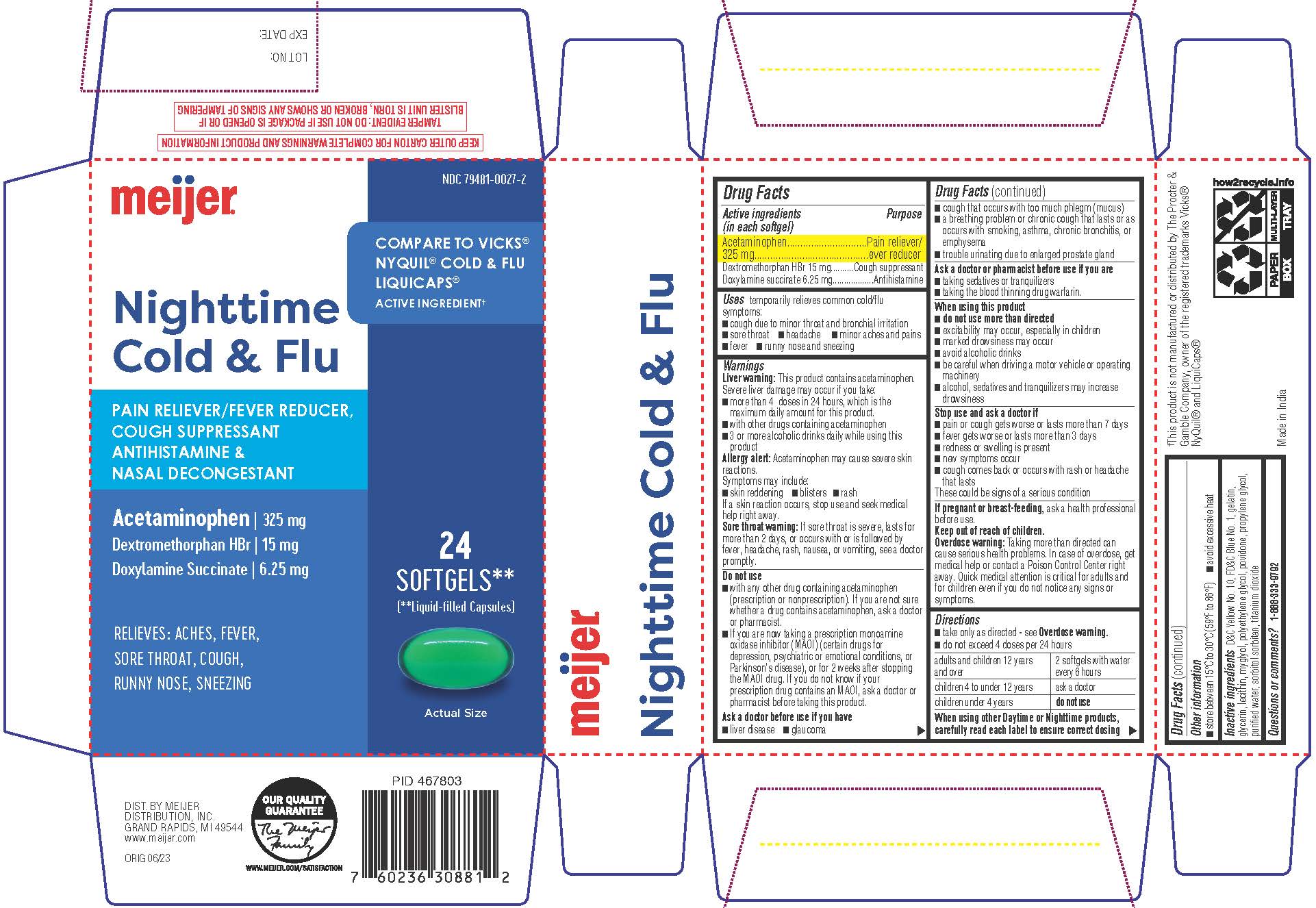 DRUG LABEL: Nightime Cold and Flu
NDC: 79481-0027 | Form: CAPSULE, LIQUID FILLED
Manufacturer: Meijer, Inc.
Category: otc | Type: HUMAN OTC DRUG LABEL
Date: 20241220

ACTIVE INGREDIENTS: ACETAMINOPHEN 325 mg/1 1; DEXTROMETHORPHAN HYDROBROMIDE 15 mg/1 1; DOXYLAMINE SUCCINATE 6.25 mg/1 1
INACTIVE INGREDIENTS: FD&C BLUE NO. 1; GELATIN; GLYCERIN; LECITHIN, SOYBEAN; POLYETHYLENE GLYCOL 400; POVIDONE; PROPYLENE GLYCOL; SORBITOL; TITANIUM DIOXIDE; D&C YELLOW NO. 10

Nighttime Cold and Flu

Active ingredients (in each softgel)

Acetaminophen 325 mg

Dextromethorphan hydrobromide 15 mg

Doxylamine succinate 6.25 mg

Purpose

Pain reliever/fever reducer

Cough suppressant

Antihistamine

Uses

temporarily relieves common cold/flu symptoms:
• cough due to minor throat and bronchial irritation
• sore throat n headache n minor aches and pains
• fever
• runny nose and sneezing

Warnings

Liver warning: This product contains acetaminophen.
Severe liver damage may occur if you take:
• more than 4 doses in 24 hours, which is the maximum daily amount for this product.
• with other drugs containing acetaminophen
• 3 or more alcoholic drinks daily while using this product

Allergy alert: Acetaminophen may cause severe skin reactions.
Symptoms may include:
• skin reddening
• blisters
• rash
If a skin reaction occurs, stop use and seek medical help right away.

Sore throat warning: If sore throat is severe, lasts for more than 2 days, or occurs with or is followed by fever, headache, rash, nausea, or vomiting, see a doctor promptly.

Do not use
• with any other drug containing acetaminophen (prescription or nonprescription). If you are not sure whether a drug contains acetaminophen, ask a doctor or pharmacist.
• If you are now taking a prescription monoamine oxidase inhibitor (MAOI) (certain drugs for depression, psychiatric or emotional conditions, or Parkinson's disease), or for 2 weeks after stopping the MAOI drug. If you do not know if your prescription drug contains an MAOI, ask a doctor or pharmacist before taking this product.

Ask a doctor before use if you have
• liver disease
• glaucoma
• cough that occurs with too much phlegm (mucus)
• a breathing problem or chronic cough that lasts or as occurs with smoking, asthma, chronic bronchitis, or emphysema
• trouble urinating due to enlarged prostate gland

Ask a doctor or pharmacist before use if you are
• taking sedatives or tranquilizers
• taking the blood thinning drug warfarin.

When using this product
• do not use more than directed
• excitability may occur, especially in children
• marked drowsiness may occur n avoid alcoholic drinks
• be careful when driving a motor vehicle or operating machinery
• alcohol, sedatives and tranquilizers may increase drowsiness

Stop use and ask a doctor if
• pain or cough gets worse or lasts more than 7 days
• fever gets worse or lasts more than 3 days
• redness or swelling is present
• new symptoms occur
• cough comes back or occurs with rash or headache that lasts
These could be signs of a serious condition

PREGNANCY OR BREAST FEEDING

If pregnant or breast-feeding, ask a health professional before use.

Keep out of reach of children.

OVERDOSAGE

Overdose warning: Taking more than directed can cause serious health problems. In case of overdose, get medical help or contact a Poison Control Center right away. Quick medical attention is critical for adults and for children even if you do not notice any signs or symptoms.

Directions

- take only as directed - see Overdose warning.
- do not exceed 4 doses per 24 hours

adults & children 12 years & over | 2 softgels with water every 6 hours
children 4 to under 12 years | ask a doctor
children under 4 years | do not use

When using other Daytime or Nighttime products, carefully read each label to ensure correct dosing

Other information

• store between 15°C to 30°C (59°F to 86°F)
• avoid excessive heat

Inactive Ingredients

D&C Yellow No. 10, FD&C Blue No. 1, gelatin, glycerin, lecithin, myglyol, polyethylene glycol, povidone, propylene glycol, purified water, sorbitol sorbitan, titanium dioxide

Questions or comments?

1-888-333-9792